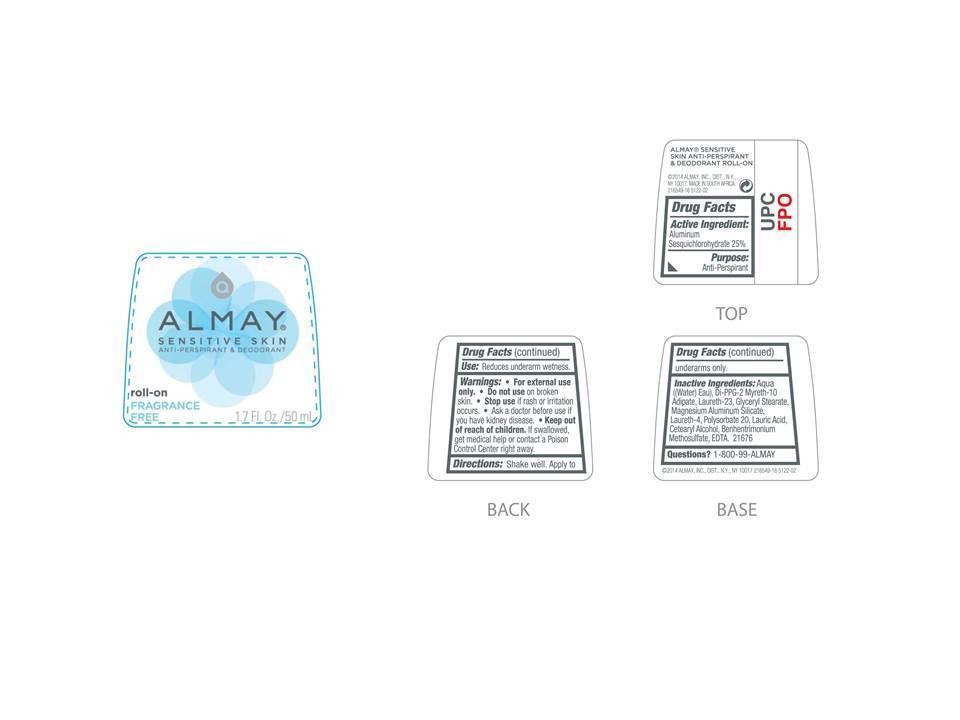 DRUG LABEL: Almay Sensitive Skin Antiperspirant - Deodorant
NDC: 0311-0585 | Form: LIQUID
Manufacturer: Almay, Inc
Category: otc | Type: HUMAN OTC DRUG LABEL
Date: 20131209

ACTIVE INGREDIENTS: ALUMINUM SESQUICHLOROHYDRATE 0.25 g/1 mL
INACTIVE INGREDIENTS: WATER; DI-PPG-2 MYRETH-10 ADIPATE; LAURETH-23; GLYCERYL MONOSTEARATE; MAGNESIUM ALUMINUM SILICATE; LAURETH-4; POLYSORBATE 20; LAURIC ACID; CETOSTEARYL ALCOHOL; BEHENTRIMONIUM METHOSULFATE; EDETIC ACID

Almay Sensitive Skin Antiperspirant - Deodorant – Fragrance Free

Drug Facts Active Ingredient

Aluminum sesquichlorohydrate 25%

Purpose

Antiperspirant

Use

- Reduces underarm wetness

Warnings:

For external use only.

Do not use on broken skin

Ask a doctor before use if you have kidney disease

Stop use if rash or irriation occurs

Keep out of reach of children.

If swallowed, get medical help or contact a Poison Control Center right away.

Directions

Apply to underarms only.

Inactive Ingredients

aqua((water) eau), di-ppg-2-myreth-10 adipate, laureth-23, glyceryl stearate, magnesium aluminum silicate, laureth-4, polysorbate 20, lauric acid, cetearyl alcohol, behentrimonium methosulfate, edta

Questions

1-800-99-ALMAY